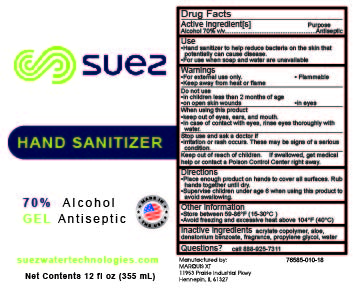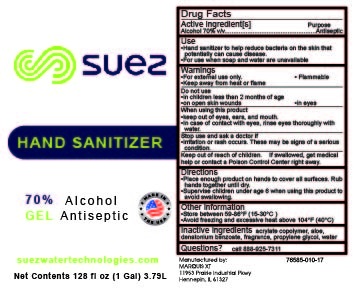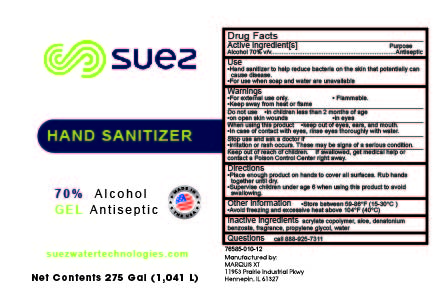 DRUG LABEL: SUEZ Gel Formula
NDC: 80896-010 | Form: GEL
Manufacturer: SUEZ Water Technologies & Solutions
Category: otc | Type: HUMAN OTC DRUG LABEL
Date: 20201023

ACTIVE INGREDIENTS: ALCOHOL 70 mL/100 mL
INACTIVE INGREDIENTS: PROPYLENE GLYCOL 1 mL/100 mL; LINALOOL, (+)- 0.3 mL/100 mL; WATER; METHACRYLIC ACID - ETHYL ACRYLATE COPOLYMER (4500 MPA.S) 1.1 mL/100 mL; ALOE VERA LEAF 0.01 mL/100 mL; DENATONIUM BENZOATE ANHYDROUS 0.00035 mL/100 mL; CUMINYL ACETALDEHYDE 0.3 mL/100 mL

Active Ingredient(s)

Alcohol 70% v/v. Purpose: Antiseptic

Purpose

Antiseptic, Hand Sanitizer

Use

Hand Sanitizer to help reduce bacteria on the skin that potentially can cause disease.

For use when soap and water are not available.

Warnings

For external use only. Flammable. Keep away from heat or flame

Do not use

- in children less than 2 months of age
- on open skin wounds
- in eyes

When using this product keep out of eyes, ears, and mouth. In case of contact with eyes, rinse eyes thoroughly with water.
Stop use and ask a doctor if irritation or rash occurs. These may be signs of a serious condition.
Keep out of reach of children. If swallowed, get medical help or contact a Poison Control Center right away.

Stop use and ask a doctor if irritation or rash occurs. These may be signs of a serious condition.

Keep out of reach of children. If swallowed, get medical help or contact a Poison Control Center right away.

Directions

- Place enough product on hands to cover all surfaces. Rub hands together until dry.
- Supervise children under 6 years of age when using this product to avoid swallowing.

Other information

- Store between 15-30C (59-86F)
- Avoid freezing and excessive heat above 104 F (40C)

Inactive ingredients

acrylate copolymer, aloe, denatonium benzoate, fragrance, glycerin, water

Package Label - Principal Display Panel

80896-010 Gel 10